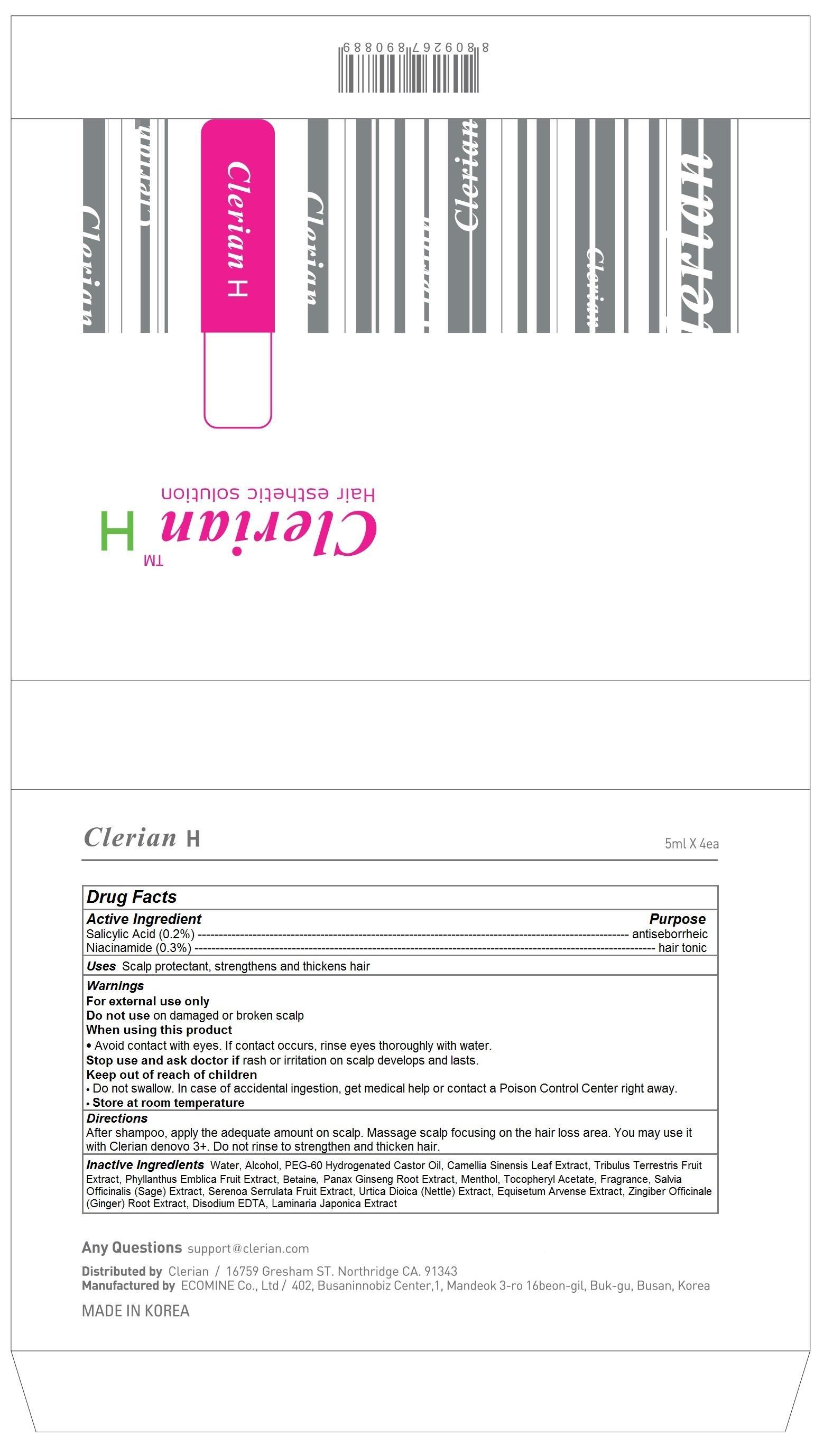 DRUG LABEL: Clerian H
NDC: 69767-102 | Form: LIQUID
Manufacturer: CLERIAN, INC.
Category: otc | Type: HUMAN OTC DRUG LABEL
Date: 20150420

ACTIVE INGREDIENTS: Salicylic Acid 0.2 1/5 mL; Niacinamide 0.3 1/5 mL
INACTIVE INGREDIENTS: WATER; ALCOHOL; PEG-60 HYDROGENATED CASTOR OIL; GREEN TEA LEAF; TRIBULUS TERRESTRIS FRUIT; PHYLLANTHUS EMBLICA FRUIT; BETAINE; ASIAN GINSENG; MENTHOL; .ALPHA.-TOCOPHEROL ACETATE; SALVIA OFFICINALIS ROOT; SAW PALMETTO; URTICA DIOICA LEAF; EQUISETUM ARVENSE BRANCH; ginger; EDETATE DISODIUM; LAMINARIA JAPONICA

Clerian H